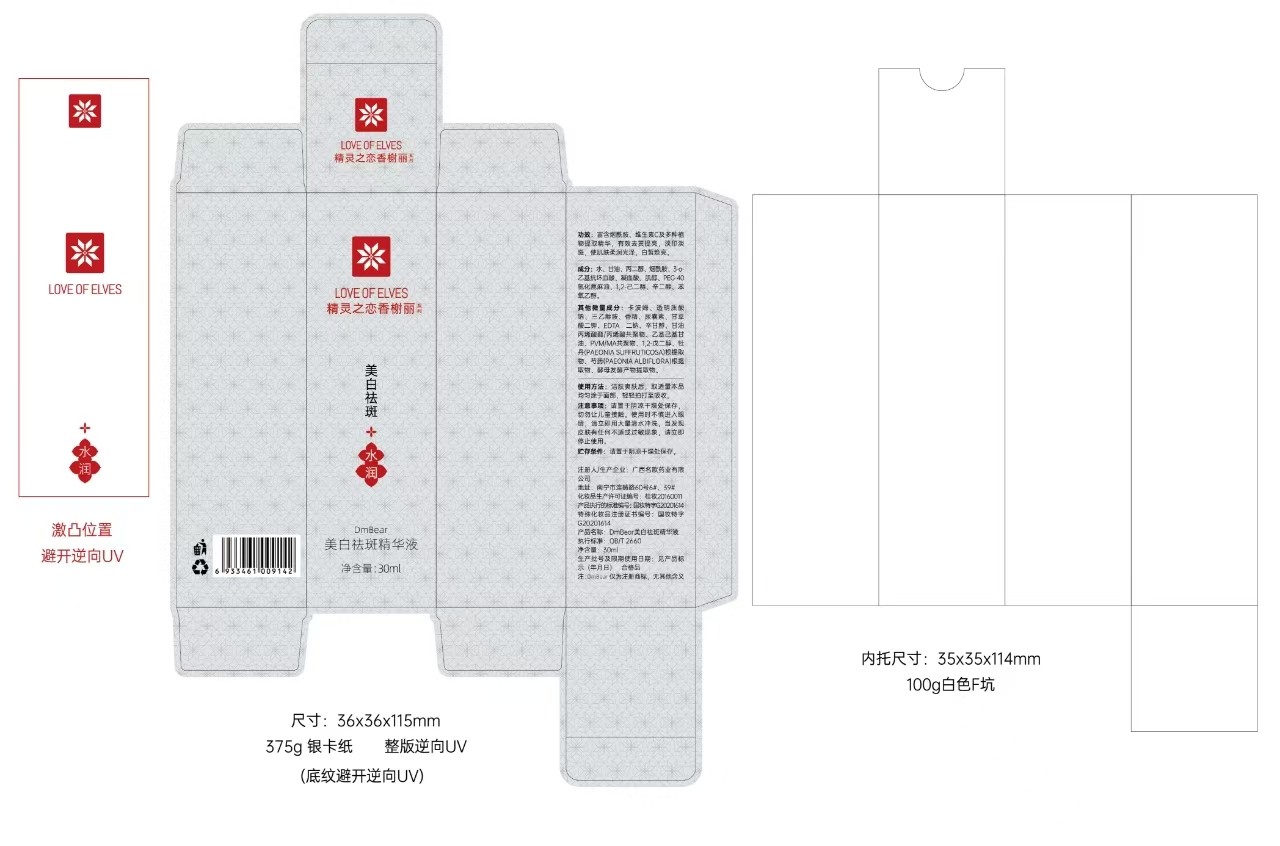 DRUG LABEL: Whitening and anti-freckle essence
NDC: 84372-056 | Form: LIQUID
Manufacturer: Shenzhen Zhumeng Times Technology Co., Ltd.
Category: otc | Type: HUMAN OTC DRUG LABEL
Date: 20240910

ACTIVE INGREDIENTS: NIACINAMIDE 1 g/1 g
INACTIVE INGREDIENTS: WATER

Active ingredients

NIACINAMIDE 3%...... Whitening treatment

Purpose

to Whitening the skin, and nurture the skin barrier.

Uses

Skin regimen is key. Most effective when applied correctly, faithfully, and consistent. Apply a small amount as a thin layer on the affected area twice daily.

Warnings

For external use only

Do not use on damaged or broken skin

When using this product keep out of eyes. Rinse with water to remove.

Stop use and ask a doctor if rash occurs

Keep out of reach of children.lf swallowed, get medical help or contact a Poison Control Center right away.

Dosage and administration

For external use only.

Do not use

Stop use and ask a doctor if

When using section

When using this product keep out of eyes. Rinse with water to remove.

Keep out of reach of children.

If sxralowed, get medical help or contact a Poison Conirol Cenler ngiht away.

Inactive ingredients

AQUA,PROPYLENE GLYCOL,ASCORBIC ACID,NIACINAMIDE,CETEARYL ALCOHOL,ETHYLHEXYL PALMITATE,CETEARYL ALCOHOL,CETEARYL GLUCOSIDE,ERYTHRITOL,GLYCERYL STEARATE,PEG-100 STEARATE,CYCLOPENTASILOXANE,CYCLOHEXASILOXANE,DIMETHICONE,PENTYLENE GLYCOL,CAPRYLHYDROXAMIC ACID,GLYCERYL CAPRYLATE,CARBOMER,METHYLPARABEN,TRIETHANOLAMINE,SODIUM HYALURONATE,DISODIUM EDTA

stop use

on broken or irritated scalp

RECENT MAJOR CHANGES

Package